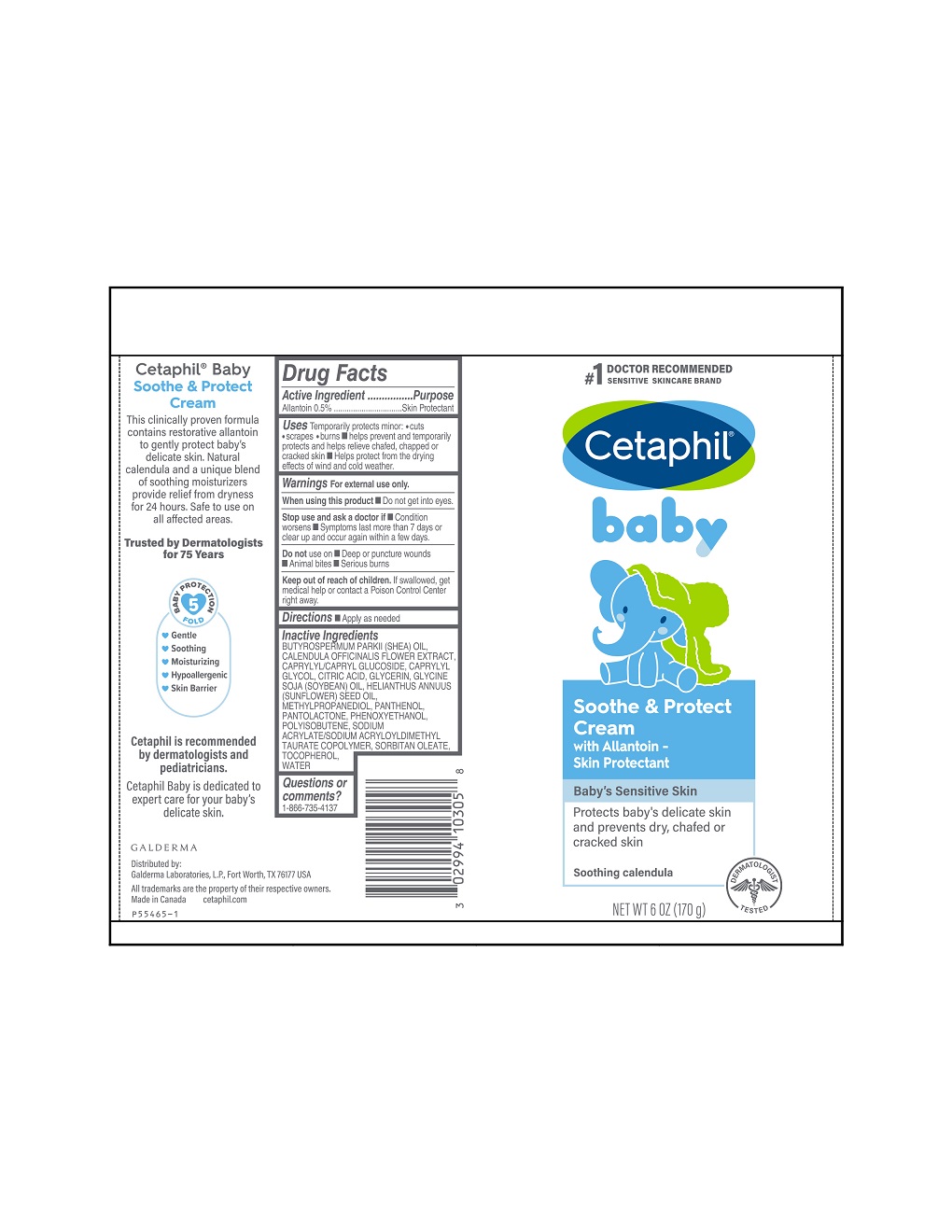 DRUG LABEL: Cetaphil Baby Soothe and Protect Cream
NDC: 0299-4103 | Form: CREAM
Manufacturer: Galderma Laboratories, L.P.
Category: otc | Type: HUMAN OTC DRUG LABEL
Date: 20231122

ACTIVE INGREDIENTS: Allantoin 5 mg/1 g
INACTIVE INGREDIENTS: Sheanut Oil; Calendula Officinalis Flower; Caprylyl Glycol; Caprylyl/Capryl Oligoglucoside; Citric Acid Monohydrate; Glycerin; Soybean Oil; Sunflower Oil; Methylpropanediol; Panthenol; Pantolactone, (R)-; Phenoxyethanol; Polyisobutylene (1000 Mw); Sodium Acrylate/Sodium Acryloyldimethyltaurate Copolymer (4000000 Mw); Tocopherol; Water; Sorbitan Monooleate

Drug Facts

Active ingredients......Purpose

Allantoin 0.5%......Skin Protectant

Uses

Temporarily protects minor: ●cuts
●scrapes ●burns ■helps prevent and temporarily
protects and helps relieve chafed, chapped or
cracked skin ■Helps protect from the drying
effects of wind and cold weather.

Warnings

For external use only.

When using this product ■ Do not get into eyes.

Stop use and ask a Doctor if ● condition worsens ● symptoms last more than 7 days or clear up and occur again within a few days.

Do not use on ■Deep or puncture wounds
■Animal bites ■Serious burns

Keep out of reach of children. If swallowed, get medical help or contact a Poison Control Center right away.

Directions

■Apply as needed

Inactive Ingredients

BUTYROSPERMUM PARKII (SHEA) OIL, CALENDULA OFFICINALIS FLOWER EXTRACT, CAPRYLYL/CAPRYL GLUCOSIDE, CAPRYLYL GLYCOL, CITRIC ACID, GLYCERIN, GLYCINE SOJA (SOYBEAN) OIL, HELIANTHUS ANNUUS (SUNFLOWER) SEED OIL, METHYLPROPANEDIOL, PANTHENOL, PANTOLACTONE, PHENOXYETHANOL, POLYISOBUTENE, SODIUM ACRYLATE/SODIUM ACRYLOYLDIMETHYL TAURATE COPOLYMER, SORBITAN OLEATE, TOCOPHEROL, WATER

Questions or comments?

1-866-735-4137

Distributed By:
Galderma Laboratories, L.P.
Fort Worth, TX 76177 USA

All trademarks are the property of their respective owners

Made in Canada

cetaphil.com

PRINCIPLE DISPLAY PANEL - 6 oz tube

#1 Doctor Recommended
Sensitive Skincare Brand
Cetaphil®

baby

Soothe & Protect
Cream
with Allantoin -
Skin Protectant

Baby's Sensitive Skin

Protects baby's delicate skin
and prevents dry, chafed or
cracked skin

Soothing calendula

(SEAL) Dermatologist tested
NET WT 6 oz (170 g)